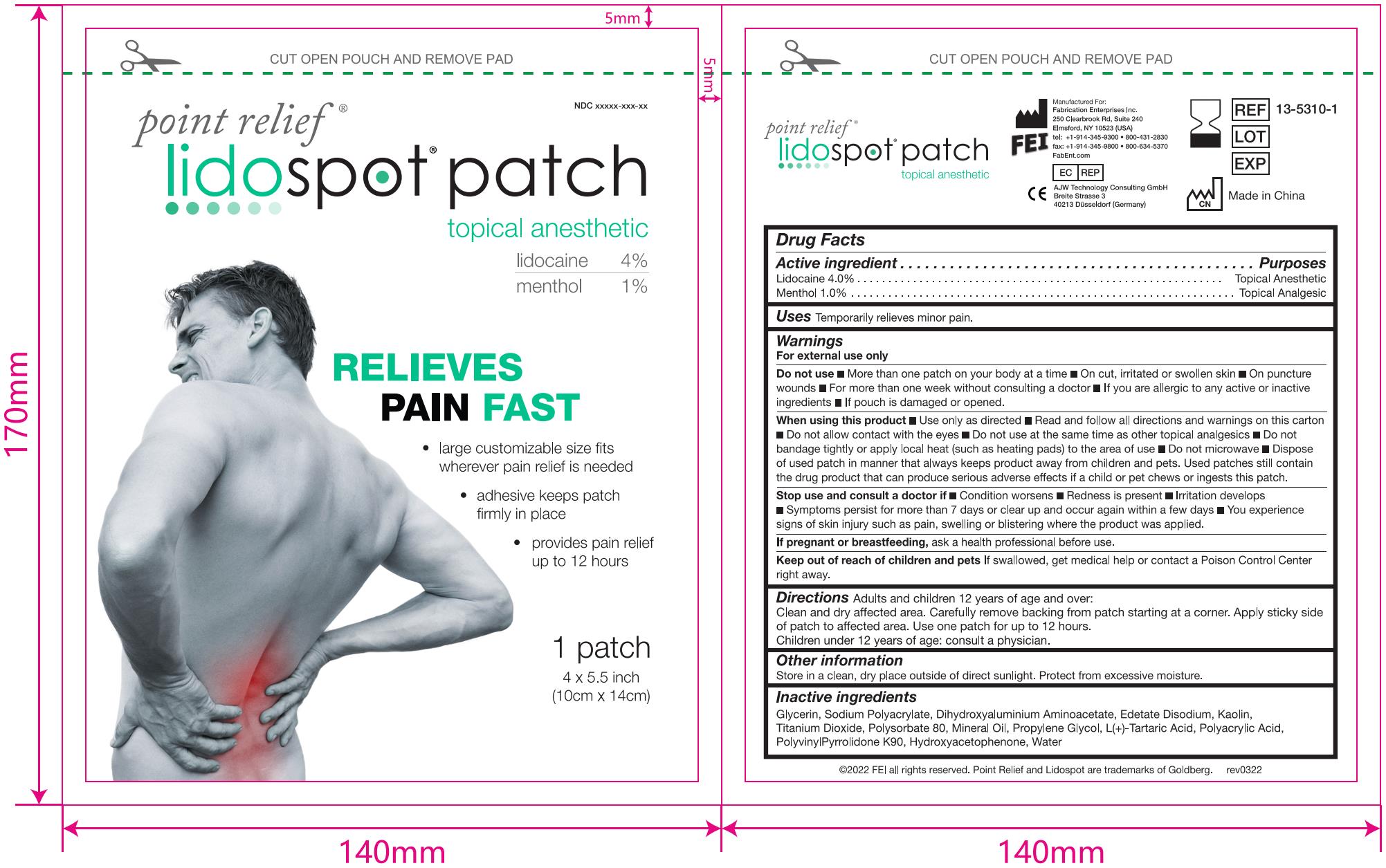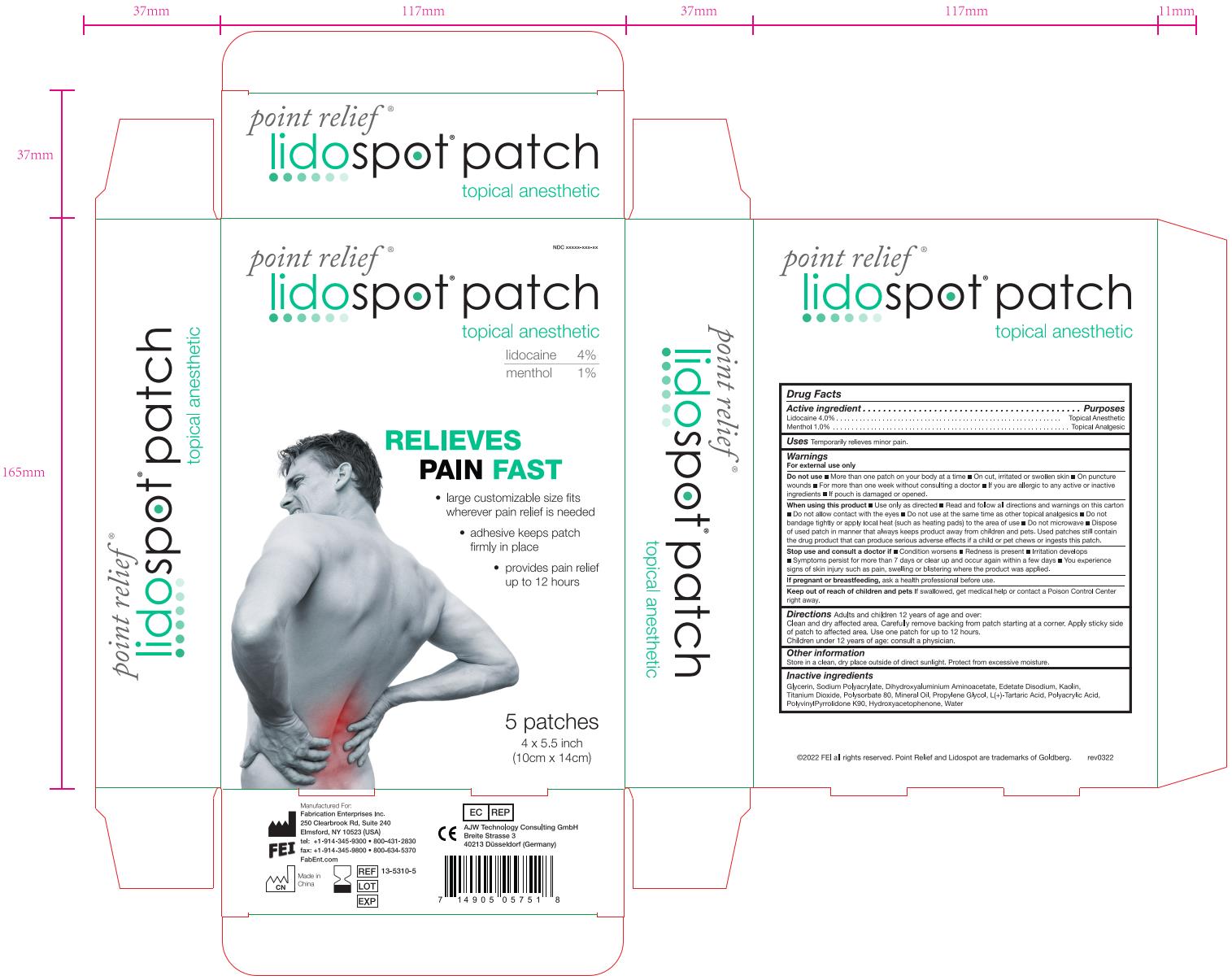 DRUG LABEL: Point relief Lidospot
NDC: 51452-173 | Form: PATCH
Manufacturer: Fabrication Enterprises
Category: otc | Type: HUMAN OTC DRUG LABEL
Date: 20220405

ACTIVE INGREDIENTS: MENTHOL 0.03 g/3 g; LIDOCAINE 0.12 g/3 g
INACTIVE INGREDIENTS: KAOLIN; TARTARIC ACID; WATER; DIHYDROXYALUMINUM AMINOACETATE ANHYDROUS; PROPYLENE GLYCOL; POLYACRYLIC ACID (250000 MW); SODIUM POLYACRYLATE (2500000 MW); TITANIUM DIOXIDE; MINERAL OIL; POLYSORBATE 80; GLYCERIN; EDETATE DISODIUM; POVIDONE K90; HYDROXYACETOPHENONE

FEI LIDOCAINE&MENTHOL PAIN RELIEF GEL-PATCH, 5 Patches

Active ingredient

Lidocaine 4.0% w/w ...... Purpose: Topical anesthetic

Menthol 1.0% w/w ...... Purpose: Topical analgesic

Purposes

Topical anesthetic (Lidocaine)

Topical analgesic (Menthol)

Uses

Temporarily relieves minor pain

Warnings

For external use only

When using this product

- Use only as directed
- Read and follow all directions and warnings on this carton
- Do not allow contact with the eyes
- Do not use at the same time as other analgesics
- Do not bandage tightly or apply local heat (such as heating pads) to the area of use
- Do not microwave
- Dispose of used patch in manner that always keeps product away from children and pets. Used patches still contain the drug product that can produce serious adverse effects if a child or pet chews or ingests this patch.

Do not use

- More than one patch on your body at a time
- On cut, irritated or swollen skin
- On puncture wounds
- For more than one week without consulting a doctor
- If you are allergic to any active or inactive ingredients
- If pouch is damaged or opened.

Stop use and consult a doctor if

- Condition worsen
- Redness is present
- Irritation develops
- Symptoms persist for more than 7 days or clear up and occur again within a few days
- You experience signs of skin injury such as pain, swelling or blistering where the product applied.

If pregnant or breastfeeding,

ask a health professional before use.

Keep out of reach of children and pets

If swallowed, get medical help or contact a Poison Control Center right away.

Directions

Adult and Children 12 years of age and over:

Clean and dry affected area. Carefully remove backing from patch starting at a corner. Apply stickly side of patch to affected area. Use one patch for up to 12 hours.

Children under 12 years of age: Consult a physician.

Inactive ingredients

Glycerin, Sodium Polyacrylate, Dihydroxyaluminium Aminoacetate, Edetate Disodium, Kaolin, Titanium Dioxide, Polysorbate 80, Mineral Oil, Propylene Glycol, L(+)-Tartaric Acid, Polyacrylic Acid, PolyvinylPyrrolidone K90, Hydroxyacetophenone, Water

Other information

Store in a clean, dry place outside of direct sunlight. Protect from excessive moisture.